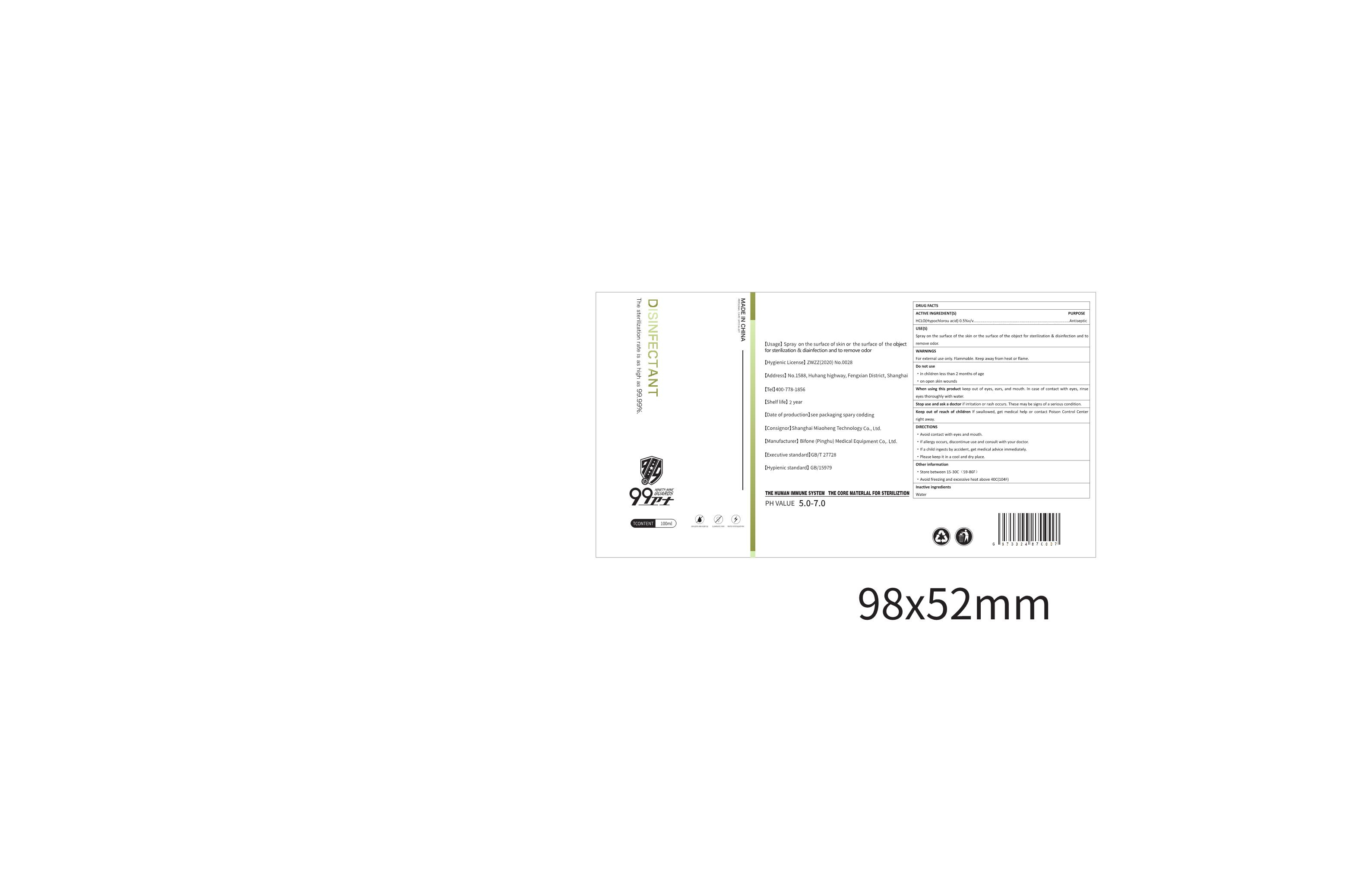 DRUG LABEL: Disinfectant
NDC: 94973-001 | Form: LIQUID
Manufacturer: Bifone (pinghu) Medical Equipment Co., Ltd
Category: otc | Type: HUMAN OTC DRUG LABEL
Date: 20201116

ACTIVE INGREDIENTS: HYPOCHLOROUS ACID 5 mg/100 mL
INACTIVE INGREDIENTS: WATER

USE(S)

Spray on the surface of the skin or the surface of the object for sterilization & disinfection and to remove odor.

WARNINGS

For external use only. Flammable.Keep away from heat or flame.

DO NOT USE

in children less than 2 months of age

on open skin wounds

When using this product keep out of eves, ears, and mouth. ln case of contact with eyes, rinseeyes thoroughly with water.

Stop use and ask a doctor if irritation or rash occurs. These may be signs of a serious condition.

Keep out of reach of children lf swallowed, get medical help or contact Poison Control Center right away.

PURPOSE

Disinfection
Sterilization

ACTIVE INGREDIENT

HCLO(Hypochlorou acid)0.5%

Other information

Store between 15-30°C(59-86°F）
Avoid freezing and excessive heat above 40°C(104°F)

INACTIVE INGREDIENT

Water

DIRECTIONS

Avoid contact with eyes and mouth.
lf allergy occurs, discontinue use and consult with your doctor.
lf a child ingests by accident, get medical advice immediately.
Please keep it in a cool and dry place.